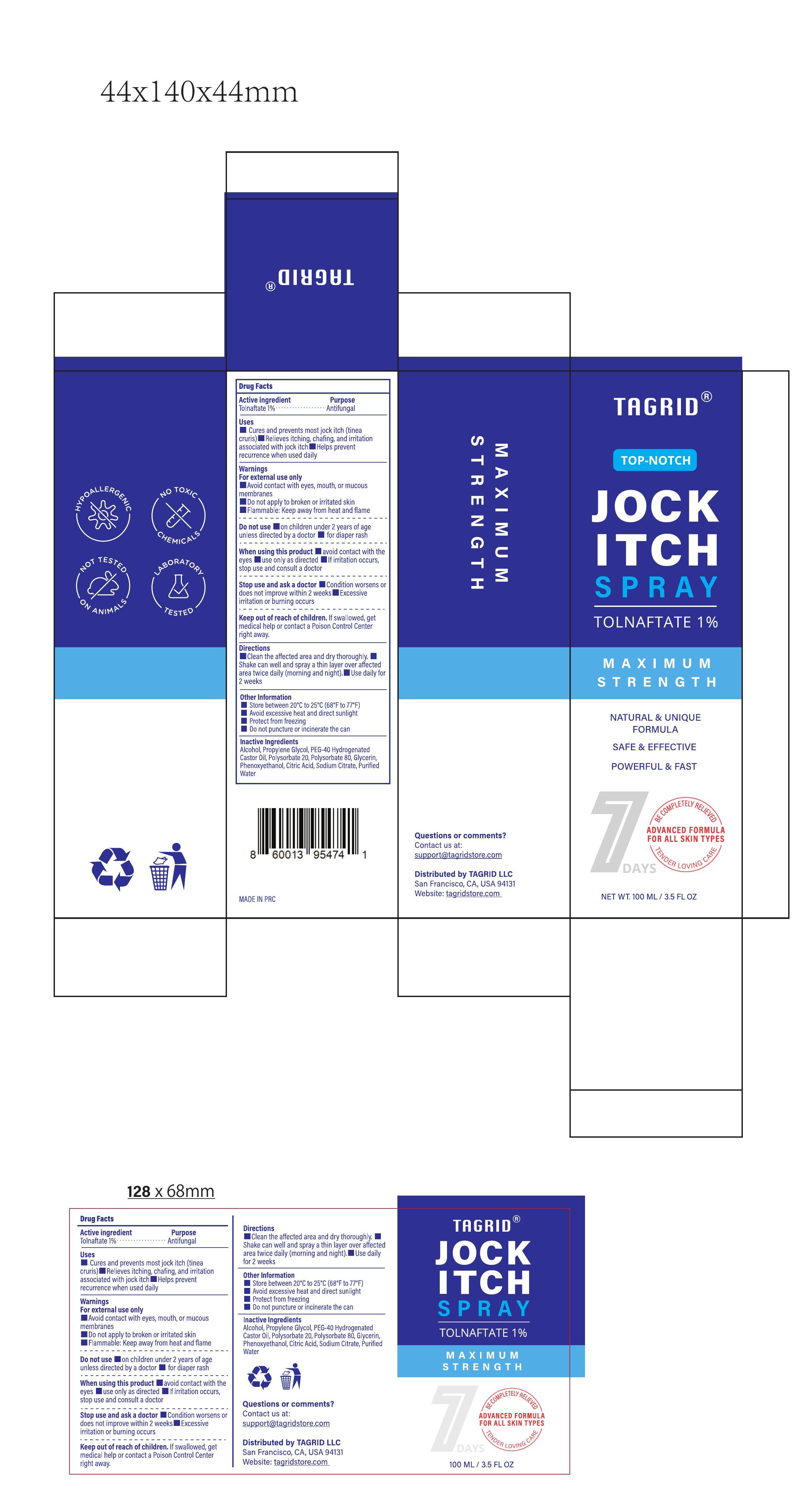 DRUG LABEL: Tagrid Jock Itch
NDC: 85384-0009 | Form: SPRAY
Manufacturer: TAGRID LLC
Category: otc | Type: HUMAN OTC DRUG LABEL
Date: 20250521

ACTIVE INGREDIENTS: TOLNAFTATE 10 mg/1 mL
INACTIVE INGREDIENTS: GLYCERIN; PHENOXYETHANOL; PEG-40 HYDROGENATED CASTOR OIL; POLYSORBATE 80; POLYSORBATE 20; SODIUM CITRATE; CITRIC ACID; WATER; ALCOHOL; PROPYLENE GLYCOL

Initial Drug Listing-Tagrid Jock Itch Spray Tolnaftate 1%

ACTIVE INGREDIENT

Tolnaftate

PURPOSE

Antifungal

INDICATIONS AND USAGE

■ Cures and prevents most jock itch (tinea cruris)
■ Relieves itching, chafing, and irritation associated with jock itch
■ Helps prevent recurrence when used daily

WARNINGS

For external use only

Avoid contact with eyes, mouth, or mucous
membranes
Do not apply to broken or irritated skin
Flammable: Keep away from heat and flame

DO NOT USE

■ on children under 2 years of age unless directed by a doctor
■ for diaper rash

Stop use and ask a doctor

Condition worsens or does not improve within 2 weeks
Excessive irritation or burning occurs

Keep out of reach of children.

If swallowed, get medical help or contact a Poison Control Center right away.

Directions
Clean the affected area and dry thoroughly.
Shake can well and spray a thin layer over affected area twice daily (morning and night).

Use daily for 2 weeks

Other Information
Store between 20°C to 25°C (68°F to 77°F)
Avoid excessive heat and direct sunlight
Protect from freezing
Do not puncture or incinerate the can

Questions or comments?
Contact us at:
support@tagridstore.com

Distributed by TAGRID LLC
San Francisco, CA, USA 94131
Website: tagridstore.com

Inactive Ingredients:
Alcohol, Propylene Glycol, PEG-40 Hydrogenated,Castor Oil, Polysorbate 20, Polysorbate 80, Glycerin,
Phenoxyethanol, Citric Acid, Sodium Citrate, Purified Water